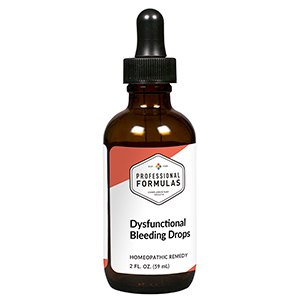 DRUG LABEL: Dysfunctional Bleeding Drops
NDC: 63083-2138 | Form: LIQUID
Manufacturer: Professional Complementary Health Formulas
Category: homeopathic | Type: HUMAN OTC DRUG LABEL
Date: 20190815

ACTIVE INGREDIENTS: BOS TAURUS HYPOTHALAMUS 6 [hp_X]/59 mL; BEEF LIVER 6 [hp_X]/59 mL; BOS TAURUS OVARY 6 [hp_X]/59 mL; BOS TAURUS PITUITARY GLAND, POSTERIOR 6 [hp_X]/59 mL; BOS TAURUS SPLEEN 6 [hp_X]/59 mL; SUS SCROFA UTERUS 6 [hp_X]/59 mL; CHASTE TREE FRUIT 8 [hp_X]/59 mL; COFFEA ARABICA SEED, ROASTED 8 [hp_X]/59 mL; CALENDULA OFFICINALIS FLOWERING TOP 9 [hp_X]/59 mL; GOLDENSEAL 9 [hp_X]/59 mL; CAPSELLA BURSA-PASTORIS WHOLE 12 [hp_X]/59 mL; CHAMAELIRIUM LUTEUM ROOT 12 [hp_X]/59 mL; SILICON DIOXIDE 12 [hp_X]/59 mL; TRIFOLIUM PRATENSE FLOWER 12 [hp_X]/59 mL; VIBURNUM OPULUS BARK 12 [hp_X]/59 mL; APIS MELLIFERA 30 [hp_X]/59 mL; SELENICEREUS GRANDIFLORUS STEM 30 [hp_X]/59 mL; COLLINSONIA CANADENSIS ROOT 30 [hp_X]/59 mL; GELSEMIUM SEMPERVIRENS ROOT 30 [hp_X]/59 mL; STRYCHNOS NUX-VOMICA SEED 30 [hp_X]/59 mL; VERATRUM ALBUM ROOT 30 [hp_X]/59 mL
INACTIVE INGREDIENTS: ALCOHOL; WATER

C138

ACTIVE INGREDIENTS

Hypothalamus 6X
Liver 6X
Ovary 6X
Pituitary 6X
Spleen 6X
Uterus 6X
Agnus castus 8X
Coffea tosta 8X
Calendula officinalis 9X
Hydrastis canadensis 9X
Capsella bursa-pastoris 12X
Endometritis tuberculosa 12X
Helonias luteum 12X
Silicea 12X
Trifolium pratense 12X
Viburnum opulus 12X
Apis mellifica 30X
Cactus grandiflorus 30X
Collinsonia canadensis 30X
Gelsemium sempervirens 30X
Nux vomica 30X
Veratrum album 30X

QUESTIONS

Professional Formulas

PO Box 2034 Lake Oswego, OR 97035

INDICATIONS

For the temporary relief of occasional mild spotting or menstrual irregularity.*

PURPOSE

*Claims based on traditional homeopathic practice, not accepted medical evidence. Not FDA evaluated.

WARNINGS

Any significant vaginal bleeding or change in menstrual pattern requires evaluation by a doctor. Keep out of the reach of children. In case of overdose, get medical help or contact a poison control center right away. If pregnant or breastfeeding, ask a healthcare professional before use.

Keep out of the reach of children.

PREGNANCY OR BREAST FEEDING

If pregnant or breastfeeding, ask a healthcare professional before use.

DIRECTIONS

Place drops under tongue 30 minutes before/after meals. Adults and children 12 years and over: Take 10 drops up to 3 times per day. Consult a physician for use in children under 12 years of age.

OTHER INFORMATION

Tamper resistant. If seal is broken, do not use. After opening, close container tightly and store at room temperature away from heat.

INACTIVE INGREDIENTS

20% ethanol, purified water.

LABEL

Est 1985

Professional Formulas

Complementary Health

Dysfunctional Bleeding Drops

Homeopathic Remedy

2 FL. OZ. (59 mL)